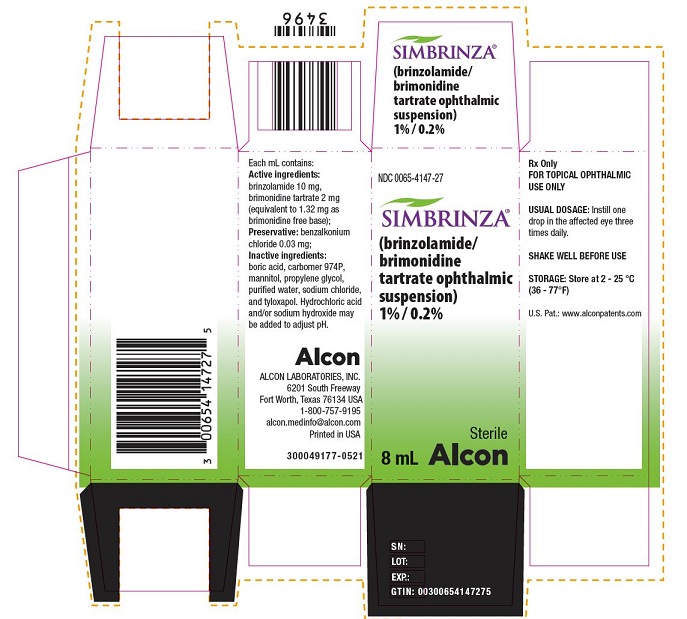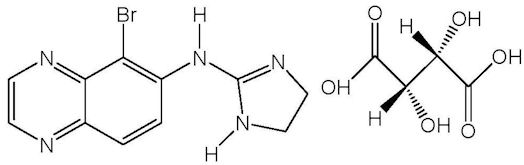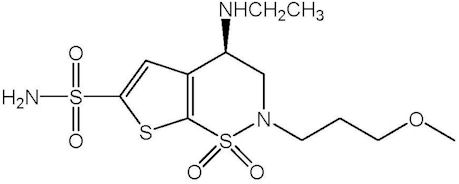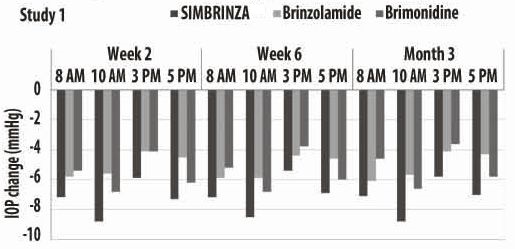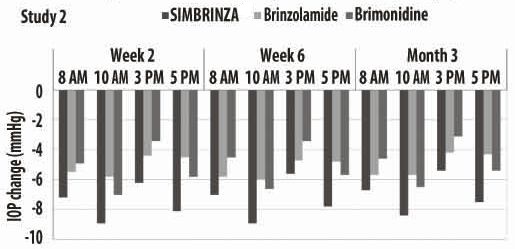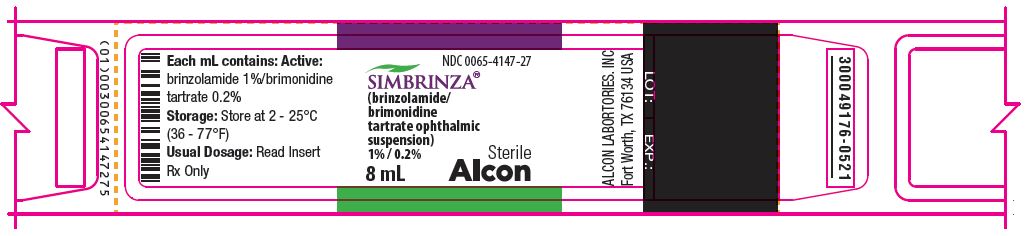 DRUG LABEL: SIMBRINZA
NDC: 0065-4147 | Form: SUSPENSION/ DROPS
Manufacturer: Alcon Laboratories, Inc.
Category: prescription | Type: HUMAN PRESCRIPTION DRUG LABEL
Date: 20250311

ACTIVE INGREDIENTS: Brinzolamide 10 mg/1 mL; Brimonidine Tartrate 2 mg/1 mL
INACTIVE INGREDIENTS: Benzalkonium Chloride; Boric Acid; Carbomer Homopolymer Type B (allyl Pentaerythritol Crosslinked); Mannitol; Propylene Glycol; Water; Sodium Chloride; Tyloxapol; Hydrochloric Acid; Sodium Hydroxide

HIGHLIGHTS OF PRESCRIBING INFORMATION

These highlights do not include all the information needed to use SIMBRINZA® safely and effectively. See full prescribing information for SIMBRINZA.
SIMBRINZA® (brinzolamide and brimonidine tartrate ophthalmic suspension) 1%/0.2%, for topical ophthalmic use
Initial U.S. Approval: 2013

1 INDICATIONS AND USAGE

SIMBRINZA is a combination of brinzolamide, a carbonic anhydrase inhibitor, and brimonidine tartrate, an alpha adrenergic agonist, indicated for the reduction of elevated intraocular pressure (IOP) in patients with open-angle glaucoma or ocular hypertension. (1)

RECENT MAJOR CHANGES

Warnings and Precautions,
Sulfonamide Hypersensitivity Reactions (5.1) 5/2023

2 DOSAGE AND ADMINISTRATION

Shake well before use. Instill one drop in the affected eye(s) three times daily. If more than one topical ophthalmic drug is being used, the drugs should be administered at least five minutes apart. (2)

3 DOSAGE FORMS & STRENGTHS

Ophthalmic suspension containing 1% (10 mg/mL) brinzolamide and 0.2% (2 mg/mL) brimonidine tartrate. (3)

4 CONTRAINDICATIONS

- Hypersensitivity to any component of this product. (4.1)
- Neonates and infants (under the age of two years). (4.2)

5 WARNINGS AND PRECAUTIONS

- Potential for sulfonamide hypersensitivity reactions because of the brinzolamide component (5.1)
- Potential for corneal endothelium cell loss (5.2)
- Severe renal impairment may limit the metabolism of the brinzolamide component (5.3)

6 ADVERSE REACTIONS

Most common adverse reactions occurring in approximately 3% to 5% of patients included blurred vision, eye irritation, dysgeusia (bad taste), dry mouth, eye allergy. (6.1)
To report SUSPECTED ADVERSE REACTIONS, contact Alcon Laboratories, Inc. at 1-800-757-9195 or FDA at 1-800-FDA-1088 or www.fda.gov/medwatch.

7 DRUG INTERACTIONS

- Oral Carbonic Anhydrase Inhibitors (7.1)
- High-dose Salicylate Therapy (7.2)
- Central Nervous System Depressants (7.3)
- Antihypertensives/Cardiac Glycosides (7.4)
- Tricyclic Antidepressants (7.5)
- Monoamine Oxidase (MAO) Inhibitors (7.6)

FULL PRESCRIBING INFORMATION

1 INDICATIONS AND USAGE

SIMBRINZA (brinzolamide/brimonidine tartrate ophthalmic suspension) 1%/0.2% is a fixed combination of a carbonic anhydrase inhibitor and an alpha 2 adrenergic receptor agonist indicated for the reduction of elevated intraocular pressure (IOP) in patients with open-angle glaucoma or ocular hypertension.

2 DOSAGE AND ADMINISTRATION

The recommended dose is one drop of SIMBRINZA in the affected eye(s) three times daily. Shake well before use. SIMBRINZA ophthalmic suspension may be used concomitantly with other topical ophthalmic drug products to lower IOP. If more than one topical ophthalmic drug is being used, the drugs should be administered at least five (5) minutes apart.

3 DOSAGE FORMS & STRENGTHS

Ophthalmic suspension containing 1% (10 mg/mL) brinzolamide and 0.2% (2 mg/mL) brimonidine tartrate.

4 CONTRAINDICATIONS

4.1 Hypersensitivity

SIMBRINZA is contraindicated in patients who are hypersensitive to any component of this product.

4.2 Neonates and Infants (under the age of two years)

SIMBRINZA is contraindicated in neonates and infants (under the age of two years) [see Use in Specific Populations (8.4)].

5 WARNINGS AND PRECAUTIONS

5.1 Sulfonamide Hypersensitivity Reactions

SIMBRINZA contains brinzolamide, a sulfonamide, and although administered topically is absorbed systemically. Therefore, the same types of adverse reactions that are attributable to sulfonamides may occur with topical administration of SIMBRINZA. Fatalities have occurred due to severe reactions to sulfonamides including Stevens-Johnson syndrome, toxic epidermal necrolysis, fulminant hepatic necrosis, agranulocytosis, aplastic anemia, and other blood dyscrasias. Sensitization may recur when a sulfonamide is re-administered irrespective of the route of administration. If signs of serious reactions or hypersensitivity occur, discontinue the use of this preparation immediately. [see Adverse Reactions (6.2) and Patient Counseling Information (17)].

5.2 Corneal Endothelium

Carbonic anhydrase activity has been observed in both the cytoplasm and around the plasma membranes of the corneal endothelium. There is an increased potential for developing corneal edema in patients with low endothelial cell counts. Caution should be used when prescribing SIMBRINZA to this group of patients.

5.3 Severe Renal Impairment

SIMBRINZA has not been specifically studied in patients with severe renal impairment (CrCl less than 30 mL/min). Since brinzolamide and its metabolite are excreted predominantly by the kidney, SIMBRINZA is not recommended in such patients.

5.4 Acute Angle-Closure Glaucoma

The management of patients with acute angle-closure glaucoma requires therapeutic interventions in addition to ocular hypotensive agents. SIMBRINZA has not been studied in patients with acute angle-closure glaucoma.

5.5 Contact Lens Wear

The preservative in SIMBRINZA, benzalkonium chloride, may be absorbed by soft contact lenses. Contact lenses should be removed during instillation of SIMBRINZA but may be reinserted 15 minutes after instillation [see Patient Counseling Information (17)].

5.6 Severe Cardiovascular Disease

Brimonidine tartrate, a component of SIMBRINZA, has a less than 5% mean decrease in blood pressure two hours after dosing in clinical studies; caution should be exercised in treating patients with severe cardiovascular disease.

5.7 Severe Hepatic Impairment

Because brimonidine tartrate, a component of SIMBRINZA, has not been studied in patients with hepatic impairment, caution should be exercised in such patients.

5.8 Potentiation of Vascular Insufficiency

Brimonidine tartrate, a component of SIMBRINZA, may potentiate syndromes associated with vascular insufficiency. SIMBRINZA should be used with caution in patients with depression, cerebral or coronary insufficiency, Raynaud’s phenomenon, orthostatic hypotension, or thromboangiitis obliterans.

5.9 Contamination of Topical Ophthalmic Products After Use

There have been reports of bacterial keratitis associated with the use of multiple-dose containers of topical ophthalmic products. These containers have been inadvertently contaminated by patients who, in most cases, had a concurrent corneal disease or a disruption of the ocular epithelial surface [see Patient Counseling Information (17)].

6 ADVERSE REACTIONS

6.1 Clinical Trials Experience

Because clinical trials are conducted under widely varying conditions, adverse reaction rates observed in the clinical trials of a drug cannot be directly compared to the rates in the clinical trials of another drug and may not reflect the rates observed in practice.
SIMBRINZA
In two clinical trials of three months duration 435 patients were treated with SIMBRINZA, and 915 were treated with the two individual components. The most frequently reported adverse reactions in patients treated with SIMBRINZA occurring in approximately 3% to 5% of patients in descending order of incidence were blurred vision, eye irritation, dysgeusia (bad taste), dry mouth, and eye allergy. Rates of adverse reactions reported with the individual components were comparable. Treatment discontinuation, mainly due to adverse reactions, was reported in 11% of SIMBRINZA patients.
Other adverse reactions that have been reported with the individual components during clinical trials are listed below.
Brinzolamide 1%
In clinical studies of brinzolamide ophthalmic suspension 1%, the most frequently reported adverse reactions reported in 5% to 10% of patients were blurred vision and bitter, sour or unusual taste. Adverse reactions occurring in 1% to 5% of patients were blepharitis, dermatitis, dry eye, foreign body sensation, headache, hyperemia, ocular discharge, ocular discomfort, ocular keratitis, ocular pain, ocular pruritus and rhinitis.
The following adverse reactions were reported at an incidence below 1%: allergic reactions, alopecia, chest pain, conjunctivitis, diarrhea, diplopia, dizziness, dry mouth, dyspnea, dyspepsia, eye fatigue, hypertonia, keratoconjunctivitis, keratopathy, kidney pain, lid margin crusting or sticky sensation, nausea, pharyngitis, tearing and urticaria.
Brimonidine Tartrate 0.2%
In clinical studies of brimonidine tartrate 0.2%, adverse reactions occurring in approximately 10% to 30% of the subjects, in descending order of incidence, included oral dryness, ocular hyperemia, burning and stinging, headache, blurring, foreign body sensation, fatigue/drowsiness, conjunctival follicles, ocular allergic reactions, and ocular pruritus.
Reactions occurring in approximately 3% to 9% of the subjects, in descending order included corneal staining/erosion, photophobia, eyelid erythema, ocular ache/pain, ocular dryness, tearing, upper respiratory symptoms, eyelid edema, conjunctival edema, dizziness, blepharitis, ocular irritation, gastrointestinal symptoms, asthenia, conjunctival blanching, abnormal vision and muscular pain.
The following adverse reactions were reported in less than 3% of the patients: lid crusting, conjunctival hemorrhage, abnormal taste, insomnia, conjunctival discharge, depression, hypertension, anxiety, palpitations/arrhythmias, nasal dryness and syncope.

6.2 Postmarketing Experience

Brinzolamide
The following adverse reactions have been identified during postapproval use of brinzolamide containing products.
Because these reactions are reported voluntarily from a population of uncertain size, it is not always possible to reliably estimate their frequency or establish a causal relationship to drug exposure.
Serious skin and subcutaneous tissue reactions such as Stevens-Johnson syndrome (SJS) and toxic epidermal necrolysis (TEN) may occur with the use of brinzolamide due to the sulfonamide component [see Warnings and Precautions (5.1) and Patient Counseling Information Sulfonamide Reactions (17)].
Brimonidine Tartrate
The following reactions have been identified during postmarketing use of brimonidine tartrate ophthalmic solutions in clinical practice. Because they are reported voluntarily from a population of unknown size, estimates of frequency cannot be made. The reactions, which have been chosen for inclusion due to either their seriousness, frequency of reporting, possible causal connection to brimonidine tartrate ophthalmic solutions, or a combination of these factors, include: bradycardia, hypersensitivity, iritis, keratoconjunctivitis sicca, miosis, nausea, skin reactions (including erythema, eyelid pruritus, rash, and vasodilation), and tachycardia.
Apnea, bradycardia, coma, hypotension, hypothermia, hypotonia, lethargy, pallor, respiratory depression, and somnolence have been reported in infants receiving brimonidine tartrate ophthalmic solutions [see Contraindications (4.2)].

7 DRUG INTERACTIONS

7.1 Oral Carbonic Anhydrase Inhibitors

There is a potential for an additive effect on the known systemic effects of carbonic anhydrase inhibition in patients receiving an oral carbonic anhydrase inhibitor and brinzolamide ophthalmic suspension 1%, a component of SIMBRINZA ophthalmic suspension. The concomitant administration of SIMBRINZA and oral carbonic anhydrase inhibitors is not recommended.

7.2 High-Dose Salicylate Therapy

Carbonic anhydrase inhibitors may produce acid-base and electrolyte alterations. These alterations were not reported in the clinical trials with brinzolamide ophthalmic suspension 1%. However, in patients treated with oral carbonic anhydrase inhibitors, rare instances of acid-base alterations have occurred with high-dose salicylate therapy. Therefore, the potential for such drug interactions should be considered in patients receiving SIMBRINZA.

7.3 Central Nervous System Depressants

Although specific drug interaction studies have not been conducted with SIMBRINZA, the possibility of an additive or potentiating effect with Central Nervous System (CNS) depressants (alcohol, opiates, barbiturates, sedatives, or anesthetics) should be considered.

7.4 Antihypertensives/Cardiac Glycosides

Because brimonidine tartrate, a component of SIMBRINZA, may reduce blood pressure, caution in using drugs such as antihypertensives and/or cardiac glycosides with SIMBRINZA is advised.

7.5 Tricyclic Antidepressants

Tricyclic antidepressants have been reported to blunt the hypotensive effect of systemic clonidine. It is not known whether the concurrent use of these agents with SIMBRINZA in humans can lead to resulting interference with the IOP lowering effect. Caution is advised in patients taking tricyclic antidepressants which can affect the metabolism and uptake of circulating amines.

7.6 Monoamine Oxidase Inhibitors

Monoamine oxidase (MAO) inhibitors may theoretically interfere with the metabolism of brimonidine tartrate and potentially result in an increased systemic side-effect such as hypotension. Caution is advised in patients taking MAO inhibitors which can affect the metabolism and uptake of circulating amines.

8 USE IN SPECIFIC POPULATIONS

8.1 Pregnancy

Developmental toxicity studies with brinzolamide in rabbits at oral doses of 1, 3, and 6 mg/kg/day (20, 60, and 120 times the recommended human ophthalmic dose) produced maternal toxicity at 6 mg/kg/day and a significant increase in the number of fetal variations, such as accessory skull bones, which was only slightly higher than the historic value at 1 and 6 mg/kg. In rats, statistically decreased body weights of fetuses from dams receiving oral doses of 18 mg/kg/day (180 times the recommended human ophthalmic dose) during gestation were proportional to the reduced maternal weight gain, with no statistically significant effects on organ or tissue development. Increases in unossified sternebrae, reduced ossification of the skull, and unossified hyoid that occurred at 6 and 18 mg/kg were not statistically significant. No treatment-related malformations were seen. Following oral administration of ^14C-brinzolamide to pregnant rats, radioactivity was found to cross the placenta and was present in the fetal tissues and blood.
Developmental toxicity studies performed in rats with oral doses of 0.66 mg brimonidine base/kg revealed no evidence of harm to the fetus. Dosing at this level resulted in a plasma drug concentration approximately 100 times higher than that seen in humans at the recommended human ophthalmic dose. In animal studies, brimonidine crossed the placenta and entered into the fetal circulation to a limited extent.
There are no adequate and well-controlled studies in pregnant women. SIMBRINZA should be used during pregnancy only if the potential benefit justifies the potential risk to the fetus.

8.2 Lactation

In a study of brinzolamide in lactating rats, decreases in body weight gain in offspring at an oral dose of 15 mg/kg/day (150 times the recommended human ophthalmic dose) were observed during lactation. No other effects were observed. However, following oral administration of ^14C-brinzolamide to lactating rats, radioactivity was found in milk at concentrations below those in the blood and plasma. In animal studies, brimonidine was excreted in breast milk.
It is not known whether brinzolamide and brimonidine tartrate are excreted in human milk following topical ocular administration. Because many drugs are excreted in human milk and because of the potential for serious adverse reactions in nursing infants from SIMBRINZA (brinzolamide/brimonidine tartrate ophthalmic suspension) 1%/0.2%, a decision should be made whether to discontinue nursing or to discontinue the drug, taking into account the importance of the drug to the mother.

8.4 Pediatric Use

The individual component, brinzolamide, has been studied in pediatric glaucoma patients 4 weeks to 5 years of age. The individual component, brimonidine tartrate, has been studied in pediatric patients 2 to 7 years old. Somnolence (50-83%) and decreased alertness was seen in patients 2 to 6 years old. SIMBRINZA ophthalmic suspension is contraindicated in children under the age of 2 years [see Contraindications (4.2)].

8.5 Geriatric Use

No overall differences in safety or effectiveness have been observed between elderly and adult patients.

10 OVERDOSAGE

Although no human data are available, electrolyte imbalance, development of an acidotic state, and possible nervous system effects may occur following an oral overdose of brinzolamide. Serum electrolyte levels (particularly potassium) and blood pH levels should be monitored.
Very limited information exists on accidental ingestion of brimonidine in adults; the only adverse event reported to date has been hypotension. Symptoms of brimonidine overdose have been reported in neonates, infants, and children receiving brimonidine as part of medical treatment of congenital glaucoma or by accidental oral ingestion. Treatment of an oral overdose includes supportive and symptomatic therapy; a patent airway should be maintained.

11 DESCRIPTION

SIMBRINZA (brinzolamide/brimonidine tartrate ophthalmic suspension) 1%/0.2% is a fixed combination of a carbonic anhydrase inhibitor and an alpha 2 adrenergic receptor agonist for topical ophthalmic use.
Brinzolamide is described chemically as: (R)-(+)-4-Ethylamino-2-(3-methoxypropyl)-3,4-dihydro-2H-thieno [3,2-e]-1,2-thiazine-6-sulfonamide-1,1- dioxide. Its empirical formula is C12H21N3O5S3, and its structural formula is:

Brinzolamide has a molecular weight of 383.5 g/mol. It is a white powder, which is insoluble in water, very soluble in methanol and soluble in ethanol.
Brimonidine tartrate is described chemically as: 5-bromo-6-(2-imidazolidinylideneamino) quinoxaline L-tartrate. Its empirical formula of C11H10BrN5 – C4H6O6 and its structural formula is:

Brimonidine tartrate has a molecular weight of 442.2 g/mol. It is a white to yellow powder that is soluble in water (34 mg/mL) at pH 6.5.
SIMBRINZA (brinzolamide/brimonidine tartrate ophthalmic suspension) 1%/0.2% is supplied as a sterile, aqueous suspension which has been formulated to be readily suspended following shaking. It has a pH of approximately 6.5 and an osmolality of approximately 270 mOsm/kg.
Each mL of SIMBRINZA (brinzolamide/brimonidine tartrate ophthalmic suspension) 1%/0.2% contains: Active ingredients: brinzolamide 10 mg, brimonidine tartrate 2 mg (equivalent to 1.32 mg as brimonidine free base); Preservative: benzalkonium chloride 0.03 mg; Inactive ingredients: boric acid, carbomer 974P, mannitol, propylene glycol, purified water, sodium chloride and tyloxapol. Hydrochloric acid and/or sodium hydroxide may be added to adjust pH.

12 CLINICAL PHARMACOLOGY

12.1 Mechanism of Action

SIMBRINZA is comprised of two components: brinzolamide (carbonic anhydrase inhibitor) and brimonidine tartrate (alpha 2 adrenergic receptor agonist). Each of these two components decreases elevated IOP. Elevated IOP is a major risk factor in the pathogenesis of optic nerve damage and glaucomatous visual field loss. The higher the level of IOP, the greater the likelihood of glaucomatous field loss and optic nerve damage.
Brinzolamide inhibits carbonic anhydrase in the ciliary processes of the eye to decrease aqueous humor secretion, presumably by slowing the formation of bicarbonate ions with subsequent reduction in sodium and fluid transport. Brinzolamide has a peak ocular hypotensive effect occurring at 2 to 3 hours post-dosing. Fluorophotometric studies in animals and humans suggest that brimonidine tartrate has a dual mechanism of action by reducing aqueous humor production and increasing uveoscleral outflow. Brimonidine tartrate has a peak ocular hypotensive effect occurring at two hours post-dosing. The result is a reduction in intraocular pressure (IOP).

12.3 Pharmacokinetics

Following topical ocular administration, brinzolamide is absorbed into the systemic circulation. Due to its affinity for CA-II, brinzolamide distributes extensively into the Red Blood Cells (RBC) and exhibits a long half-life in whole blood (approximately 111 days). In humans, the metabolite N-desethyl brinzolamide is formed, which also binds to CA and accumulates in RBCs. This metabolite binds mainly to CA-I in the presence of brinzolamide. In plasma, both parent brinzolamide and N-desethyl brinzolamide concentrations are <10 ng/mL. Binding to plasma proteins is approximately 60%. Brinzolamide is eliminated predominantly in the urine as unchanged drug. N-Desethyl brinzolamide is also found in the urine along with lower concentrations of the N-desmethoxypropyl and O-desmethyl metabolites.
After ocular administration of a 0.2% solution of brimonidine tartrate, plasma concentrations peaked within 1 to 4 hours and declined with a systemic half-life of approximately 3 hours. In humans, systemic metabolism of brimonidine is extensive. It is metabolized primarily by the liver. Urinary excretion is the major route of elimination of the drug and its metabolites. Approximately 87% of an orally-administered radioactive dose was eliminated within 120 hours, with 74% found in the urine.
In humans, a study was conducted to evaluate the pharmacokinetics of the fixed combination of brinzolamide/brimonidine tartrate 1%/0.2% ophthalmic suspension. Healthy volunteers were randomly assigned to receive twice or three times a day either the fixed combination, or either of its individual components, brinzolamide or brimonidine. Subjects who were assigned to the brinzolamide alone or combination arms were administered oral brinzolamide capsules for two weeks prior to beginning dosing with the topical ocular suspension. The results demonstrate that the systemic plasma exposure (AUC and Cmax) to brinzolamide and brimonidine in humans is similar after dosing with the fixed combination to that observed following dosing with the individual components.

13 NONCLINICAL TOXICOLOGY

13.1 Carcinogenesis, Mutagenesis, Impairment of Fertility

Brinzolamide caused urinary bladder tumors in female mice at oral doses of 10 mg/kg/day and in male rats at oral doses of 8 mg/kg/day in 2 year studies. Brinzolamide was not carcinogenic in male mice or female rats dosed orally for up to 2 years. The carcinogenicity appears secondary to kidney and urinary bladder toxicity. These levels of exposure cannot be achieved with topical ophthalmic dosing in humans.

The following tests for mutagenic potential of brinzolamide were negative: (1) in vivo mouse micronucleus assay; (2) in vivo sister chromatid exchange assay; and (3) Ames E. coli test. The in vitro mouse lymphoma forward mutation assay was negative in the absence of activation, but positive in the presence of microsomal activation. In this assay, there was no consistent dose-response relationship to the increased mutation frequency and cytotoxicity likely contributed to the high mutation frequency. Carbonic anhydrase inhibitors, as a class, are not mutagenic and the weight of evidence supports that brinzolamide is consistent with the class. In reproduction studies of brinzolamide in rats, there were no adverse effects on the fertility or reproductive capacity of males or females at doses up to 18 mg/kg/day (180 times the recommended human ophthalmic dose).
Brimonidine tartrate was not carcinogenic in either a 21-month mouse or 24-month rat study. In these studies, dietary administration of brimonidine tartrate at doses up to 2.5 mg/kg/day in mice and 1 mg/kg/day in rats resulted in plasma drug concentrations 80 and 120 times higher than the human plasma drug level at the recommended clinical dose, respectively. Brimonidine tartrate was not mutagenic or cytogenic in a series of in vitro and in vivo studies including the Ames test, chromosomal aberration assay in Chinese Hamster Ovary (CHO) cells, a host-mediated assay and cytogenic studies in mice, and a dominant lethal assay. In reproductive studies performed in rats with oral doses of 0.66 mg brimonidine base/kg (approximately 100 times the plasma drug concentration level seen in humans following multiple ophthalmic doses), fertility was not impaired.

14 CLINICAL STUDIES

Two clinical trials of 3 months duration were conducted in patients with open-angle glaucoma or ocular hypertension to compare the IOP-lowering effect of SIMBRINZA (brinzolamide/brimonidine tartrate ophthalmic suspension) 1%/0.2% dosed three times daily to individually administered 1% brinzolamide three times daily and 0.2% brimonidine tartrate three times daily. Mean IOP values at baseline are presented in Table 1.

Table 1. Mean (SD) IOP values at baseline
 |  | SIMBRINZA | Brinzolamide | Brimonidine
Study 1 |  | (n=209) | (n=224) | (n=216)
 | 8 AM | 26.9 (2.63) | 27.1 (2.64) | 27.0 (2.56)
 | 10 AM | 25.3 (2.76) | 25.4 (2.74) | 25.4 (2.78)
 | 3 PM | 23.7 (2.98) | 23.8 (3.24) | 24.0 (3.27)
 | 5 PM | 23.2 (3.08) | 23.6 (3.39) | 23.7 (3.30)
Study 2 |  | (n=218) | (n=229) | (n=232)
 | 8 AM | 27.2 (2.75) | 27.2 (2.72) | 27.3 (2.73)
 | 10 AM | 25.8 (3.09) | 26.0 (3.20) | 25.8 (3.02)
 | 3 PM | 24.4 (3.67) | 24.4 (3.58) | 24.0 (3.39)
 | 5 PM | 24.1 (3.71) | 24.2 (3.86) | 23.7 (3.58)

The IOP-lowering effect of SIMBRINZA ophthalmic suspension was 1 to 3 mmHg greater than monotherapy with either 1% brinzolamide or 0.2% brimonidine tartrate throughout the duration of the trials. Least Square Mean IOP (mmHg) and the results at Week 2, Week 6 and Month 3 for each study are provided in Table 2.

Table 2 Mean IOP (mmHg) by Treatment Group and Treatment Difference in Mean IOP**
 | SIMBRINZA | Brinzolamide |  | Brimonidine
Study 1 | (N=209) | (N=224) |  | (N=216)
 | Mean | Mean | Difference (95%CI)† | Mean | Difference (95%CI)†
Week 2
8 AM | 20.4 | 22.0 | -1.6 (-2.3, -0.9) | 22.4 | -2.0 (-2.7, -1.3)
10 AM | 17.1 | 20.5 | -3.4 (-4.1, -2.7) | 19.4 | -2.3 (-3.0, -1.6)
3 PM | 18.4 | 20.4 | -1.9 (-2.6, -1.3) | 20.6 | -2.2 (-2.9, -1.5)
5 PM | 16.6 | 19.7 | -3.2 (-3.9, -2.5) | 18.4 | -1.9 (-2.6, -1.2)
Week 6
8 AM | 20.4 | 21.9 | -1.5 (-2.2, -0.8) | 22.6 | -2.3 (-3.0, -1.6)
10 AM | 17.5 | 20.2 | -2.7 (-3.4, -2.0) | 19.5 | -2.0 (-2.7, -1.3)
3 PM | 18.9 | 20.2 | -1.2 (-1.9, -0.5) | 21.1 | -2.1 (-2.8, -1.4)
5 PM | 17.0 | 19.7 | -2.6 (-3.3, -1.9) | 18.6 | -1.5 (-2.2, -0.8)
Month 3
8 AM | 20.5 | 21.6 | -1.1 (-1.8, -0.4) | 23.3 | -2.8 (-3.5, -2.1)
10 AM | 17.2 | 20.4 | -3.2 (-3.9, -2.5) | 19.7 | -2.5 (-3.2, -1.8)
3 PM | 18.7 | 20.4 | -1.8 (-2.5, -1.1) | 21.3 | -2.6 (-3.3, -1.9)
5 PM | 17.0 | 20.0 | -3.0 (-3.7, -2.3) | 18.8 | -1.8 (-2.5, -1.1)
Study 2 | (N=218) | (N=229) |  | (N=232)
Week 2
8 AM | 20.5 | 22.2 | -1.7 (-2.4, -1.0) | 22.8 | -2.4 (-3.1, -1.7)
10 AM | 17.4 | 20.7 | -3.3 (-4.0, -2.6) | 19.2 | -1.8 (-2.5, -1.2)
3 PM | 18.7 | 20.5 | -1.7 (-2.4, -1.1) | 21.1 | -2.3 (-3.0, -1.6)
5 PM | 16.5 | 20.1 | -3.6 (-4.3, -2.9) | 18.3 | -1.8 (-2.4, -1.1)
Week 6
8 AM | 20.7 | 21.9 | -1.2 (-1.9, -0.5) | 23.2 | -2.5 (-3.2, -1.8)
10 AM | 17.4 | 20.5 | -3.1 (-3.8, -2.4) | 19.7 | -2.3 (-3.0, -1.6)
3 PM | 19.3 | 20.2 | -0.8 (-1.5, -0.2) | 21.2 | -1.9 (-2.6, -1.2)
5 PM | 16.9 | 19.9 | -3.0 (-3.7, -2.3) | 18.5 | -1.7 (-2.4, -1.0)
Month 3
8 AM | 21.1 | 22.0 | -1.0 (-1.7, -0.3) | 23.2 | -2.2 (-2.9, -1.5)
10 AM | 18.0 | 20.8 | -2.8 (-3.5, -2.1) | 19.9 | -1.9 (-2.6, -1.2)
3 PM | 19.5 | 20.7 | -1.2 (-1.9, -0.5) | 21.5 | -2.0 (-2.7, -1.3)
5 PM | 17.2 | 20.4 | -3.2 (-3.9, -2.5) | 18.9 | -1.7 (-2.4, -1.0)

Abbreviations: CI, 95% Confidence Interval; IOP, intraocular pressure.
**Based on the Intent-to-Treat Population defined as all patients who received study drug and completed at least 1 on-therapy study visit.
†The estimates are based on least square means derived from a linear mixed model that accounts for correlated IOP measurements within patient; Treatment difference is SIMBRINZA minus individual component. CI=95% Confidence Interval

Figures 1 and 2 present the mean of individual subject IOP changes from baseline at Week 2, Week 6, and at Month 3 based on the observed data for the intent-to-treat population.

Figure 1. Mean IOP Change from Baseline (Study 1)

Figure 2. Mean IOP Change from Baseline (Study 2)

16 HOW SUPPLIED/STORAGE AND HANDLING

SIMBRINZA (brinzolamide/brimonidine tartrate ophthalmic suspension) 1%/0.2% is supplied in white low density polyethylene (LDPE) DROP-TAINER® bottles with a natural LDPE dispensing-tip and light green polypropylene cap as follows:

8 mL in a 10 mL bottle NDC 0065-4147-27

Storage and Handling

Store SIMBRINZA at 2°C to 25°C (36°F to 77°F). After opening, SIMBRINZA can be used until the expiration date on the bottle.

17 PATIENT COUNSELING INFORMATION

Sulfonamide Hypersensitivity Reactions
Advise patients that if serious or unusual ocular or systemic reactions or signs of hypersensitivity occur, they should discontinue the use of the product and consult their physician immediately [see Warnings and Precautions (5.1) and Adverse Reactions (6.2)].

Temporary Blurred Vision
Vision may be temporarily blurred following dosing with SIMBRINZA. Care should be exercised in operating machinery or driving a motor vehicle [see Adverse Reactions (6.1)]. .

Effect on Ability to Drive and Use Machinery
As with other drugs in this class, SIMBRINZA may cause fatigue and/or drowsiness in some patients. Caution patients who engage in hazardous activities of the potential for a decrease in mental alertness.

Avoiding Contamination of the Product
Instruct patients that ocular solutions, if handled improperly or if the tip of the dispensing container contacts the eye or surrounding structures, can become contaminated by common bacteria known to cause ocular infections. Serious damage to the eye and subsequent loss of vision may result from using contaminated solutions [see Warnings and Precautions (5.9)]. Always replace the cap after using. If solution changes color or becomes cloudy, do not use. Do not use the product after the expiration date marked on the bottle.

Intercurrent Ocular Conditions
Advise patients that if they have ocular surgery or develop an intercurrent ocular condition (e.g., trauma or infection) they should immediately seek their physician's advice concerning the continued use of the present multi-dose container.

Concomitant Topical Ocular Therapy
If more than one topical ophthalmic drug is being used, the drugs should be administered at least five minutes apart [see Dosage and Administration].

Contact Lens Wear
The preservative in SIMBRINZA, benzalkonium chloride, may be absorbed by soft contact lenses. Contact lenses should be removed during instillation of SIMBRINZA, but may be reinserted 15 minutes after instillation [see Warnings and Precautions (5.5)].

©2023 Alcon Inc.
U.S. Pat.: www.alconpatents.com
Alcon
Distributed by:
ALCON LABORATORIES, INC.
Fort Worth, Texas 76134 USA

PRINCIPAL DISPLAY PANEL

NDC 0065-4147-27
SIMBRINZA®
(brinzolamide/brimonidine tartrate ophthalmic suspension) 1% / 0.2%
Sterile
8 mL
Alcon
Rx Only
FOR TOPICAL OPHTHALMIC USE ONLY
USUAL DOSAGE: Instill one
drop in the affected eye three
times daily.
SHAKE WELL BEFORE USE
STORAGE: Store at 2 - 25 °C
(36 - 77°F)
U.S. Pat.: www.alconpatents.com
Each mL contains:
Active ingredients:
brinzolamide 10 mg,
brimonidine tartrate 2 mg
(equivalent to 1.32 mg as
brimonidine free base);
Preservative: benzalkonium
chloride 0.03 mg;
Inactive ingredients:
boric acid, carbomer 974P,
mannitol, propylene glycol,
purified water, sodium chloride,
and tyloxapol. Hydrochloric acid,
and/or sodium hydroxide may
be added to adjust pH.
ALCON
ALCON LABORATORIES, INC.
6201 South Freeway
Fort Worth, Texas 76134 USA
1-800-757-9195
alcon.medinfo@alcon.com
Printed in USA
300049177-0521
SN:
LOT:
EXP:
GTIN: 00300654147275

PRINCIPAL DISPLAY PANEL
NDC 0065-4147-27
SIMBRINZA®
(brinzolamide/brimonidine tartrate ophthalmic suspension) 1% / 0.2%
Sterile
8 mL
Alcon
Alcon Laboratories, Inc
Fort Worth, TX 76134 USA
Each mL contains: Active:
brinzolamide 1%/brimonidine tartrate 0.2%
Storage: Store at 2 - 25 °C (36 - 77°F)
Usual Dosage: Read insert
Rx Only
LOT:
EXP:
300049176-0521